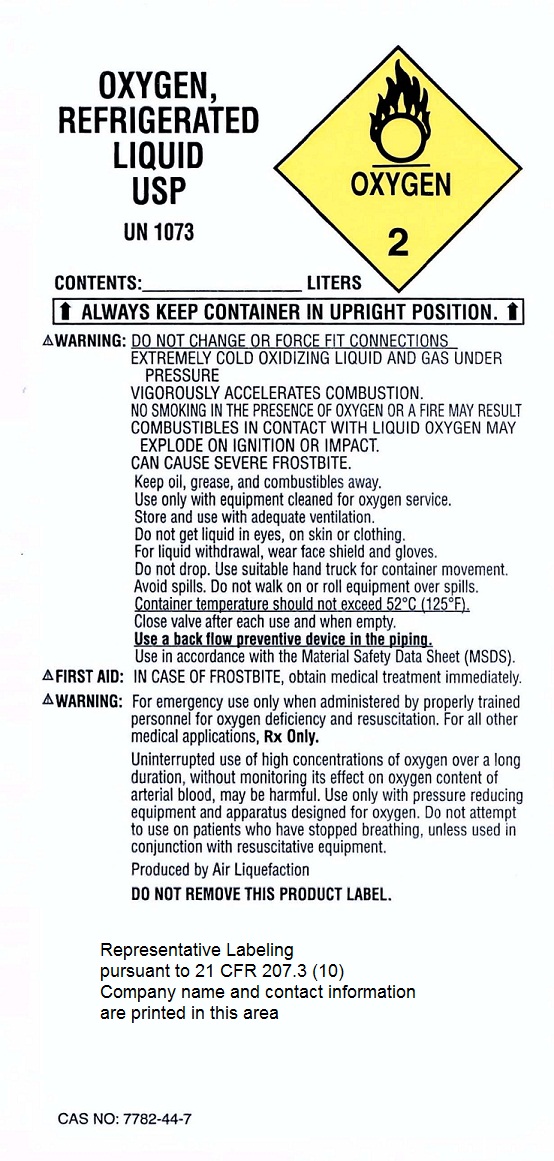 DRUG LABEL: Oxygen
NDC: 10675-002 | Form: GAS
Manufacturer: America's Healthcare At Home, Inc. 
Category: prescription | Type: HUMAN PRESCRIPTION DRUG LABEL
Date: 20110214

ACTIVE INGREDIENTS: Oxygen 99 L/100 L

Oxygen